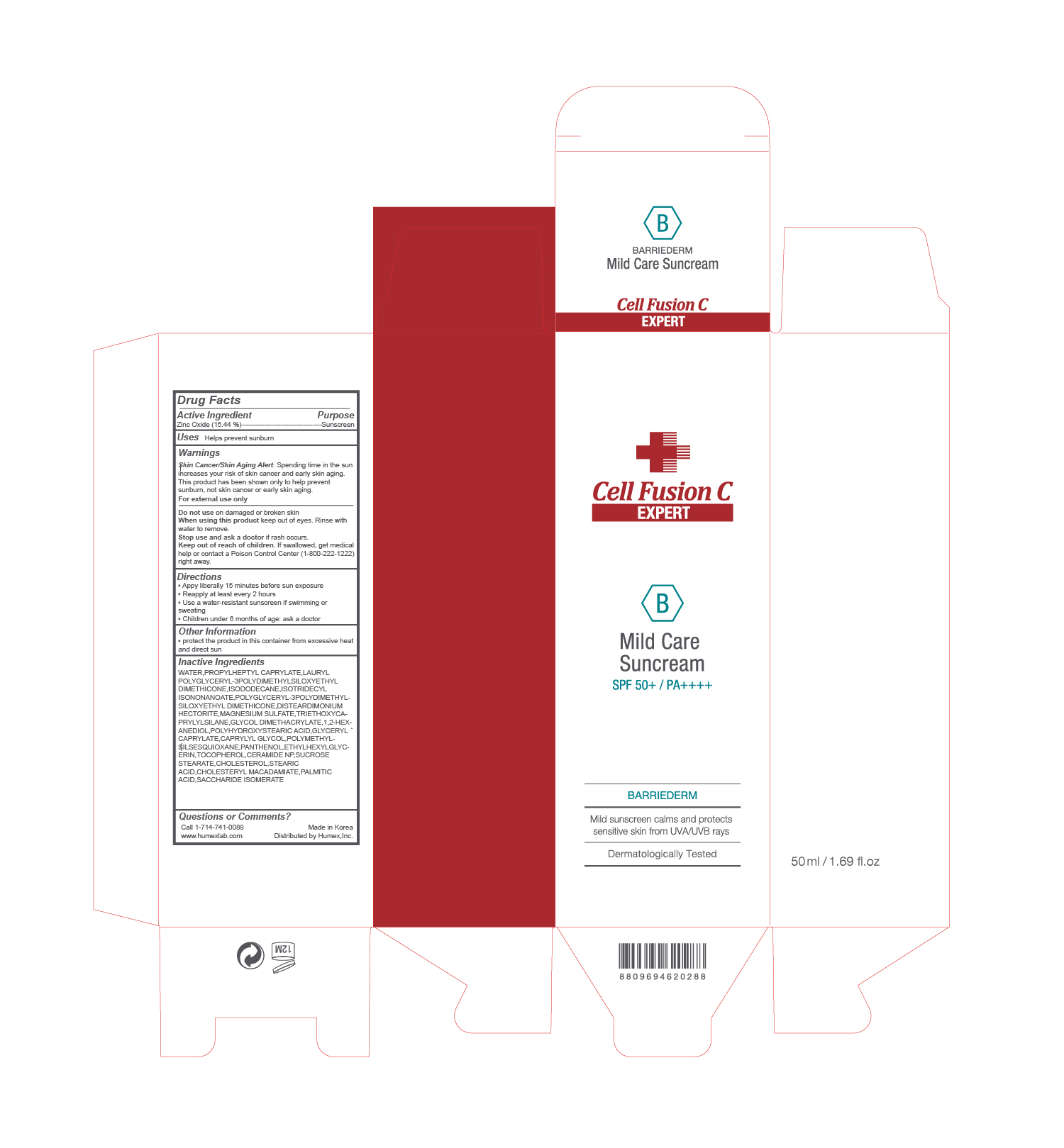 DRUG LABEL: Mild Care Suncream
NDC: 76344-8006 | Form: CREAM
Manufacturer: HUMEX,INC.
Category: otc | Type: HUMAN OTC DRUG LABEL
Date: 20230110

ACTIVE INGREDIENTS: ZINC OXIDE 15.44 g/100 mL
INACTIVE INGREDIENTS: ISOTRIDECYL ISONONANOATE 2 g/100 mL; MAGNESIUM SULFATE, UNSPECIFIED 0.8 g/100 mL; TRIETHOXYCAPRYLYLSILANE 0.63 g/100 mL; POLYMETHYLSILSESQUIOXANE (11 MICRONS) 0.1 g/100 mL; PANTHENOL 0.07 g/100 mL; ETHYLHEXYLGLYCERIN 0.04 g/100 mL; TOCOPHEROL 0.01 g/100 mL; CHOLESTERYL MACADAMIATE 0.01 g/100 mL; PALMITIC ACID 0.01 g/100 mL; SACCHARIDE ISOMERATE 0.01 g/100 mL; POLYGLYCERYL-3 POLYDIMETHYLSILOXYETHYL DIMETHICONE (4000 MPA.S) 2.39 g/100 mL; CAPRYLYL GLYCOL 0.1 g/100 mL; SUCROSE STEARATE 0.01 h/100 mL; CHOLESTEROL 0.01 g/100 mL; STEARIC ACID 0.01 g/100 mL; PROPYLHEPTYL CAPRYLATE 12.49 g/100 mL; ISODODECANE 2 g/100 mL; DISTEARDIMONIUM HECTORITE 0.8 g/100 mL; GLYCOL DIMETHACRYLATE 0.6 g/100 mL; 1,2-HEXANEDIOL 0.3 g/100 mL; POLYHYDROXYSTEARIC ACID (2300 MW) 0.16 g/100 mL; GLYCERYL CAPRYLATE 0.1 g/100 mL; CERAMIDE NP 0.01 g/100 mL

Drug Facts Active ingredient Purpose

Zinc Oxide(15.445) Sunscreen

Uses

Helps prevent sunburn

Warnings

Skin Cancer/Skin Aging Alert: Spending time in the sun increases your risk of skin cancer and early skin aging. This product has been shown only to help prevent sunburn, not skin cancer or early skin aging.

For external use only

Do not use on damaged or broken skin
When using this product keep out of eyes. Rinse with water to remove.
Stop use and ask a doctor if rash occurs.
Keep out of reach of children. If swallowed, get medical help or contact a Poison Control Center (1-800-222-1222) right away.

Directions

▪ Appy liberally 15 minutes before sun exposure
▪ Reapply at least every 2 hours
▪ Use a water-resistant sunscreen if swimming or sweating
▪ Children under 6 months of age: ask a doctor

Other Information

▪ protect the product in this container from excessive heat and direct sun

Inactive Ingredients

WATER,PROPYLHEPTYL CAPRYLATE,LAURYL POLYGLYCERYL-3POLYDIMETHYLSILOXYETHYL DIMETHICONE,ISODODECANE,ISOTRIDECYL ISONONANOATE,POLYGLYCERYL-3POLYDIMETHYLSILOXYETHYL DIMETHICONE,DISTEARDIMONIUM HECTORITE,MAGNESIUM SULFATE,TRIETHOXYCAPRYLYLSILANE,GLYCOL DIMETHACRYLATE,1,2-HEXANEDIOL,POLYHYDROXYSTEARIC ACID,GLYCERYL CAPRYLATE,CAPRYLYL GLYCOL,POLYMETHYLSILSESQUIOXANE,PANTHENOL,ETHYLHEXYLGLYCERIN,TOCOPHEROL,CERAMIDE NP,SUCROSE STEARATE,CHOLESTEROL,STEARIC ACID,CHOLESTERYL MACADAMIATE,PALMITIC ACID,SACCHARIDE ISOMERATE